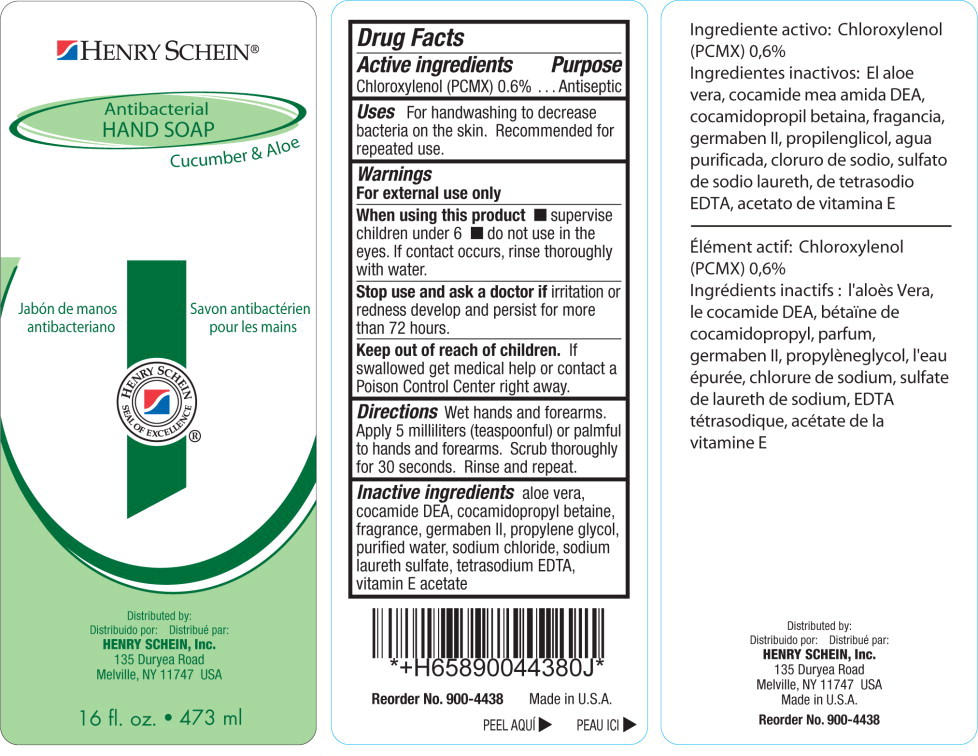 DRUG LABEL: Antibacterial Hand
NDC: 0404-4438 | Form: SOAP
Manufacturer: Henry Schein, Inc.
Category: otc | Type: HUMAN OTC DRUG LABEL
Date: 20250110

ACTIVE INGREDIENTS: CHLOROXYLENOL 6.1 g/1 L
INACTIVE INGREDIENTS: ALOE VERA LEAF; COCO DIETHANOLAMIDE; COCAMIDOPROPYL BETAINE; DIAZOLIDINYL UREA; PROPYLENE GLYCOL; WATER; SODIUM CHLORIDE; SODIUM LAURETH-3 SULFATE; EDETATE SODIUM; .ALPHA.-TOCOPHEROL ACETATE

0404-4438 Antibacterial Hand Soap- Cucumber and Aloe

Drug Facts

Active Ingredient

Chloroxylenol (PCMX) 0.6%

Purpose

Antiseptic

Uses

For handwashing to decrease bacteria on skin. Recommended for repeated use.

Warnings

For external use only.

When using this product

- supervise children under 6
- do not use in the eyes. If contact occurs, rinse thoroughly with water.

Stop use and ask doctor ifirritation or redness develop and persist for more than 72 hours.

Keep out of reach of children.If swallowed get medical help or contact a Poison Control Center right away.

Directions

Wet hands and forearms. Apply 5 milliliters (teaspoonful) or palmful to hands and forearms. Scrub thoroughly for 30 seconds. Rinse and repeat.

Inactive ingredients

aloe vera, cocamide DEA, cocamidopropyl betaine, fragrance, germaben II, propylene glycol, purified water, sodium chloride, sodium laureth sulfate, tetrasodium EDTA, vitamin E acetate

PRINCIPAL DISPLAY PANEL – 473 mL (16 fl. oz.) bottle

Henry Schein

Antibacterial

HAND SOAP

Cucumber & Aloe

Jabón de manos
antibacteriano

Savon antibactérien
pour les mains

Distributed by:
Distribuido por: Distribué par:
HENRY SCHEIN, Inc.
135 Duryea Road
Melville, NY 11747 USA

16 fl. oz. • 473 ml